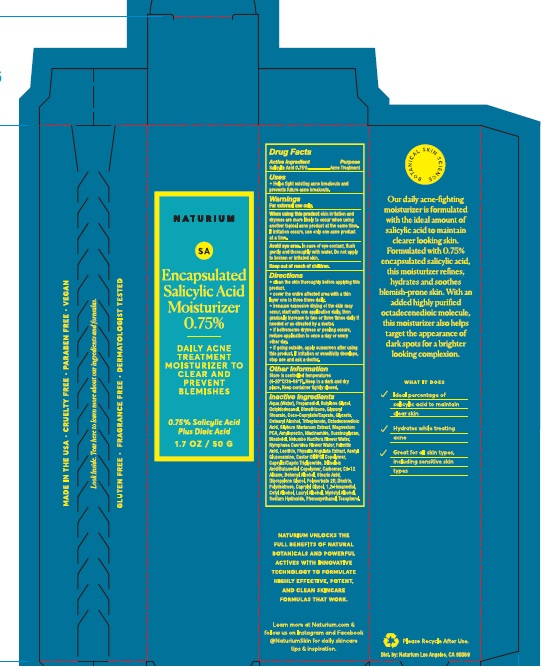 DRUG LABEL: Naturium Encapsulated Salicylic Acid Moisturizer 0.75%
NDC: 76354-121 | Form: LOTION
Manufacturer: e.l.f. Cosmetics, Inc
Category: otc | Type: HUMAN OTC DRUG LABEL
Date: 20251114

ACTIVE INGREDIENTS: SALICYLIC ACID 7.5 mg/1 g
INACTIVE INGREDIENTS: NIACINAMIDE; C9-12 ALKANE; 1,2-HEXANEDIOL; BUTYLENE GLYCOL; CETOSTEARYL ALCOHOL; TRIHEPTANOIN; OCTADECENEDIOIC ACID; MILK THISTLE; MAGNESIUM PIDOLATE; WATER; AMYLOPECTIN, UNSPECIFIED SOURCE; PROPANEDIOL; GLYCERIN; COCO-CAPRYLATE/CAPRATE; GLYCERYL MONOSTEARATE; PALMITIC ACID; MEDIUM-CHAIN TRIGLYCERIDES; ICODEXTRIN; POLYDEXTROSE; CAPRYLYL GLYCOL; CETYL ALCOHOL; MYRISTYL ALCOHOL; PHENOXYETHANOL; TOCOPHEROL; OCTYLDODECANOL; LAURYL ALCOHOL; DIMETHICONE; LEVOMENOL; LECITHIN, SOYBEAN; POLYSORBATE 20; NYMPHAEA CAERULEA FLOWER VOLATILE OIL; N-ACETYLGLUCOSAMINE; STEARIC ACID; SODIUM HYDROXIDE; NELUMBO NUCIFERA FLOWER OIL; PHYSALIS ANGULATA WHOLE; DILINOLEIC ACID/BUTANEDIOL COPOLYMER; DOCOSANOL; CARBOMER HOMOPOLYMER, UNSPECIFIED TYPE; DIPROPYLENE GLYCOL

Naturium Encapsulated Salicylic Acid Moisturizer 0.75%

Active Ingredient

Salicylic Acid 0.75%

Purpose

Acne Treatment

Uses

- Helps fight existing acne breakouts and prevents future acne breakouts.

Warnings

For external use only.

When using this product

- skin irritation and dryness are more likely to occur when using another topical acne product at the same time. If irritation occurs, use only one acne product at a time.
- Avoid eye area. In case of eye contact, flush gently and thoroughly with water. Do not apply to broken or irritated skin.

Keep out of reach of children.

If swallowed, seek medical help.

Directions

- clean the skin thoroughly before applying this product.
- cover the entire affected area with a thin layer one to three times daily.
- because excessive drying of the skin may occur, start with one application daily, then gradually increase to two or three times daily if needed or as directed by a doctor.
- if bothersome dryness or peeling occurs, reduce application to once a day or every other day.
- if going outside, apply sunscreen after using this product. If irritation or sensitivity develops, stop use and ask a doctor.

Other Information

Store in controlled temperatures (4-20°C/39-68°F). Keep in a dark and dry place. Keep container tightly closed.

Inactive Ingredients

Aqua (Water), Propanediol, Butylene Glycol, Octyldodecanol, Dimethicone, Glyceryl Stearate, Coco-Caprylate/Caprate, Glycerin, Cetearyl Alcohol, Triheptanoin, Octadecenedioic Acid, Silybum Marianum Extract, Magnesium PCA, Amylopectin, Niacinamide, Succinoglycan, Bisabolol, Nelumbo Nucifera Flower Water, Nymphaea Caerulea Flower Water, Palmitic Acid, Lecithin, Physalis Angulata Extract, Acetyl Glucosamine, Castor Oil/IPDI Copolymer, Caprylic/Capric Triglyceride, Dilinoleic Acid/Butanediol Copolymer, Carbomer, C9-12 Alkane, Behenyl Alcohol, Stearic Acid, Dipropylene Glycol, Polysorbate 20, Dextrin, Polydextrose, Caprylyl Glycol, 1,2-Hexanediol, Cetyl Alcohol, Lauryl Alcohol, Myristyl Alcohol, Sodium Hydroxide, Phenoxyethanol, Tocopherol.